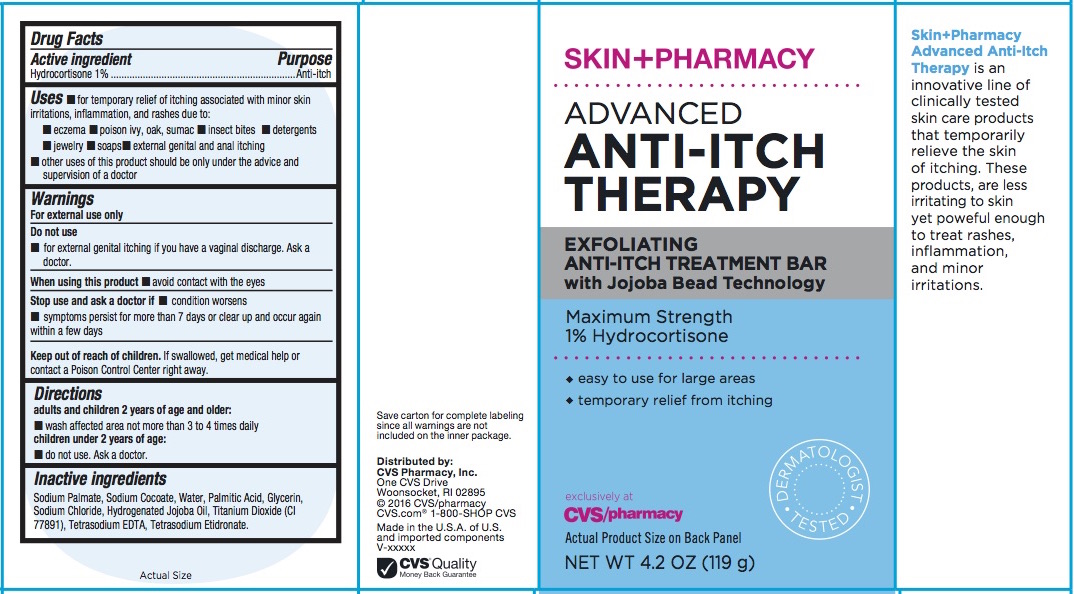 DRUG LABEL: ADVANCED ANTI-ITCH THERAPY
NDC: 69842-345 | Form: SOAP
Manufacturer: CVS Pharmacy, Inc.
Category: otc | Type: HUMAN OTC DRUG LABEL
Date: 20160614

ACTIVE INGREDIENTS: HYDROCORTISONE ACETATE 1 g/100 g
INACTIVE INGREDIENTS: TITANIUM DIOXIDE; SODIUM PALMATE; SODIUM COCOATE; PALMITIC ACID; GLYCERIN; SODIUM CHLORIDE; ETIDRONATE TETRASODIUM; EDETATE SODIUM; HYDROGENATED JOJOBA OIL; WATER

ADVANCED ANTI-ITCH THERAPY

Active Ingredient

Hydrocortisone 1%

Purpose

Anti-itch

Use

■ for temporary relief of itching associated with minor skin irritations, inflammation, and rashes due to:
■ eczema ■ poison ivy, oak, sumac ■ insect bites ■ detergents
■ jewelry ■ soaps ■ external genital and anal itching
■ other uses of this product should be only under the advice and supervision of a doctor

Warnings

For external use only

- Keep out of the reach of children.
- If swallowed, get medical help or contact a Poison Control Center immediately.

Directions

adults and children 2 years of age and older:
■wash affected area not more than 3 to 4 times daily children under 2 years of age:
■do not use. Ask a doctor.

When using this product ■ avoid contact with the eyes.

Stop use and ask a doctor if ■ condition worsens
■ symptoms persist for more than 7 days or clear up and occur again within a few days

Do not use ■ for external genital itching if you have a vaginal discharge. Ask a doctor

INACTIVE INGREDIENT

Sodium Palmate, Sodium Cocoate, Water, Palmitic Acid, Glycerin, Sodium Chloride, Hydrogenated Jojoba Oil, Titanium Dioxide (CI 77891), Tetrasodium EDTA, Tetrasodium Etidronate

Questions?

www.CVS.com

1-800-SHOP CVS